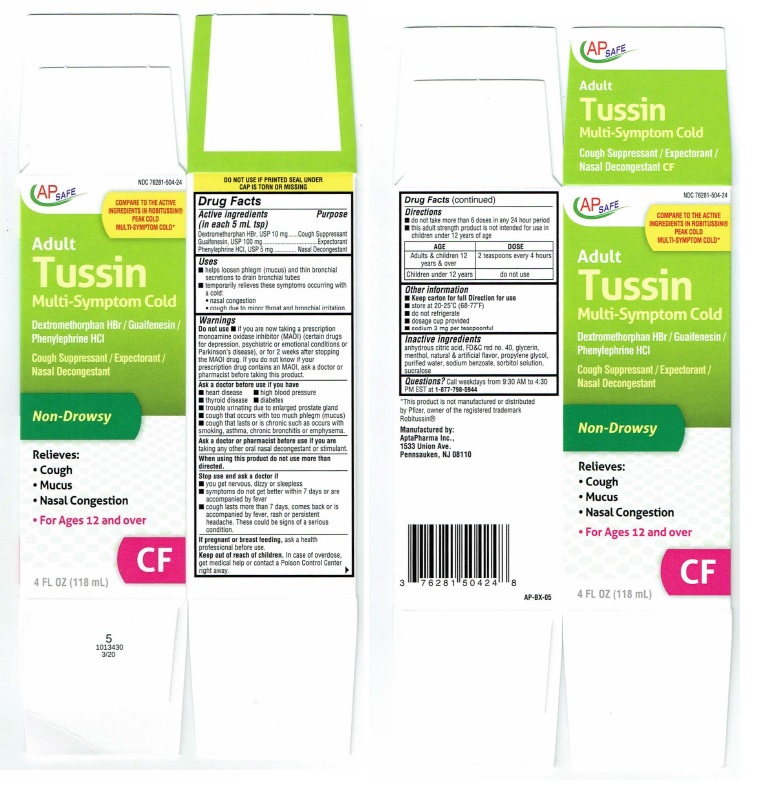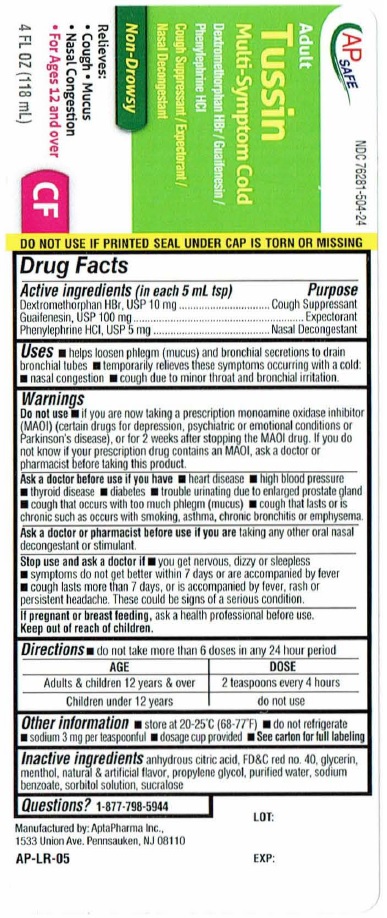 DRUG LABEL: TUSSIN CF
NDC: 76281-504 | Form: LIQUID
Manufacturer: AptaPharma Inc.
Category: otc | Type: HUMAN OTC DRUG LABEL
Date: 20251226

ACTIVE INGREDIENTS: DEXTROMETHORPHAN HYDROBROMIDE 10 mg/5 mL; GUAIFENESIN 100 mg/5 mL; PHENYLEPHRINE HYDROCHLORIDE 5 mg/5 mL
INACTIVE INGREDIENTS: ANHYDROUS CITRIC ACID; FD&C RED NO. 40; GLYCERIN; MENTHOL; PROPYLENE GLYCOL; WATER; SODIUM BENZOATE; SORBITOL SOLUTION; SUCRALOSE

Drug Facts

Active ingredients
(in each 5 mL tsp)
Dextromethorphan HBr, USP 10 mg
Guaifenesin, USP 100 mg
Phenylephrine HCL, USP 5 mg

Purpose
Dextromethorphan HBr USP ........Cough Suppressant
Guailenesin USP ..........................Expectorant
Phenylephrine HCI, USP ...............Nasal Decongestant

Uses
■ helps loosen phlegm (mucus) and thin bronchial
secretions to drain bronchial tubes
■ temporarily relieves these symptoms occurring with
a cold:

- nasal congestion
- cough due to minor throat and bronchial irritation.

Warnings
Do not use ■ if you are now taking aprescription
monoamine oxidase inhibitor (MAOI) (certain drugs
for depression, psychialric or emotional conditions or
Parkinson's disease), or for 2 weeks aMer stopping
the MAOI drug. If you do not know il your
prescription drug contains an MAOI, ask a doctor or
pharmacist before taking this product.

Ask a doctor before use if you have
■ heart disease ■ high blood pressure
■ thyroid disease ■ diabetes
■ trouble urinating due to enlarged prostate gland
■ cough that occurs with too much phlegm (mucus)
■ cough that lasts or is chronic such as occurs with
smoking, asthma, chronic bronchitis or emphysema.

Ask a doctor or pharmacist before use il you are
taking any other oral nasal decongestant or stimulant.

When using this product do not use more than
directed.

Stop use and ask a doctor if
■ you get nervous, diuy or sleepless
■ symptoms do not get better within 7 days or are
accompanied by fever
■ cough lasts more than 7 days, comes back or is
accompanied by fever, rash or persistent
headache. These could be signs ot aserious
condition.

If pregnant or breast feeding,

ask a health professional before use.

Keep out of reach of children.In case of overdose,
get medical help or contact aPoison Control Center
right away.

Directions
■ do not take more than 6 doses in any 24 hour period
■ this adult strength product is not intended for use in
children under 12 years of age

AGE | DOSE
Adults & children 12; years & over | 2 teaspoons every 4 hours
Children under 12 years | 2 teaspoons every 4 hours

Other information
■ Keep carton for full Direction for use
■ store at 20-25ºC (68-77ºF)
■ do not refrigerate
■ dosage cup provided
■ sodium 3 mg per teaspoonful

Inactive ingredients
anhydrous citric acid, FD&C red no. 40, glycerin,
menthol, natural & artificial flavor, propylene glycol,
purified water, sodium benzoate, sorbitol solution,
sucralose

QUESTIONS

Questions?Call weekdays from 9:30 AM to 4:30
PM EST at 1-877·798-5944

Product Label

AP SAFE NDC 76821-504-24

COMPARE TO THE ACTIVE

INGREDIENT IN ROBITUSSIN®

PEAK COLD

MULTI-SYMPTOM COLD*

Adult Tussin

Multi-Symptom Cold

Dextromethorphan HBr / Guaifensesin /

Phenylephrine HCL

Cough Supressant / Expectorant /

Nasal Decongestant

Non-Drowsy

Relieves:
• Cough
• Mucus
• Nasal Congestion
• For Ages 12 and over

4 FL OZ (118 mL)

CF

DO NOT USE IF PRINTED SEAL UNDER
CAP IS TORN OR MISSING

5
1013430
3/20

*This product is not manufactured or distributed
by Plizer, owner of the registered trademark
Robitussin®

Manufactured by:
AptaPharma Inc.,
1533 Union Ave,
Pennsauken, NJ 08110

Ap·BX·05

Carton

Bottle

res